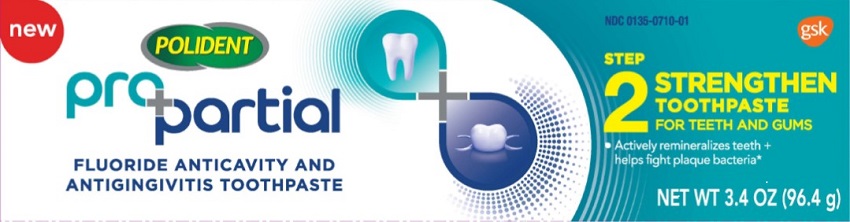 DRUG LABEL: Polident

NDC: 0135-0710 | Form: PASTE
Manufacturer: Haleon US Holdings LLC
Category: otc | Type: HUMAN OTC DRUG LABEL
Date: 20240207

ACTIVE INGREDIENTS: STANNOUS FLUORIDE 1.5 mg/1 g
INACTIVE INGREDIENTS: GLYCERIN; POLYETHYLENE GLYCOL 400; HYDRATED SILICA; SODIUM TRIPOLYPHOSPHATE ANHYDROUS; SODIUM LAURYL SULFATE; TITANIUM DIOXIDE; COCAMIDOPROPYL BETAINE; SACCHARIN SODIUM

Drug Facts

Active ingredient

Stannous fluoride 0.454% (0.15% w/v fluoride ion)

Purposes

Anticavity, Antigingivitis

Uses

- aids in the prevention of dental cavities.
- helps prevent gingivitis, an early form of gum disease.
- helps interfere with harmful effects of plaque associated with gingivitis.

Warnings

Stop use and ask a dentist if

- gingivitis, bleeding, or redness persists for more than 2 weeks.
- you have painful or swollen gums, pus from the gum line, loose teeth, or increasing spacing
- between the teeth. These may be signs or symptoms of periodontitis, a serious form of gum disease.

Keep out of reach of children under 6 years of age.

If more than used for brushing is accidentally swallowed, get medical help or contact a Poison Control Center right away.

Directions

- adults and children 2 years of age and older:
  - apply toothpaste onto a toothbrush.
  - brush teeth thoroughly, preferably after each meal at least twice a day, and not more than 3 times a day, or as directed by a dentist or doctor. Minimize swallowing. Spit out after brushing.
- to minimize swallowing for children under 6 years of age, use a pea-sized amount and supervise brushing and rinsing until good habits are established.
- children under 2 years of age:Consult a dentist or doctor.

Other information

- products containing stannous fluoride may produce surface staining of the teeth. Adequate
- toothbrushing may prevent these stains which are not harmful or permanent and may be removed by your dentist.
- this product is specially formulated to help prevent staining.
- store below 25°C (77°F)

Inactive ingredients

glycerin, PEG-8, hydrated silica, pentasodium triphosphate, flavor, sodium lauryl sulfate, titanium

dioxide, polyacrylic acid, cocamidopropyl betaine, sodium saccharin

Questions or comments?

1-866-844-2796

Additional Information

ALWAYS FOLLOW THE LABEL

Your partial can act as a bacteria magnet, attracting more odor-causing bacteria, plaque and debris that if not cleaned can damage your natural teeth.

NEW POLIDENT ProPartialis a simple 3-step range specially developed to cleanse partial dentures, help strengthen teeth, and help protect against odor-causing bacteria.

STEP 1PURIFYYour Partial with Foam Cleanser

STEP 2 STRENGHTENYour Teeth + Gums with Toothpaste

STEP 3 PROTECTYour Teeth with Mouthwash

Strengthens by remineralizing teeth, including vulnerable teeth next to the partial and helps fight plaque bacteria*.

*associated with gingivitis, an early form of gum disease

1-866-844-2796

Distributed by:

GSK Consumer Healthcare,Warren, NJ 07059

Trademarks are owned by or licensed to the GSK group of companies.

©2020 GSK group of companies or its licensor.

Made in Germany.

Best used before the end of: see end of carton.

Principal Display Panel

NDC 0135-0710-01

POLIDENT

PROPARTIAL

Fluoride Anticavity and Antigingivitis Toothpaste

new

STEP 2 STRENGTHEN TOOTHPASTE FOR TEETH AND GUMS

- Actively remineralizes teeth + helps fight plaque bacteria*

Net wt 3.4 oz (96.4 g)

62000000050516: Tube

62000000050517: Carton